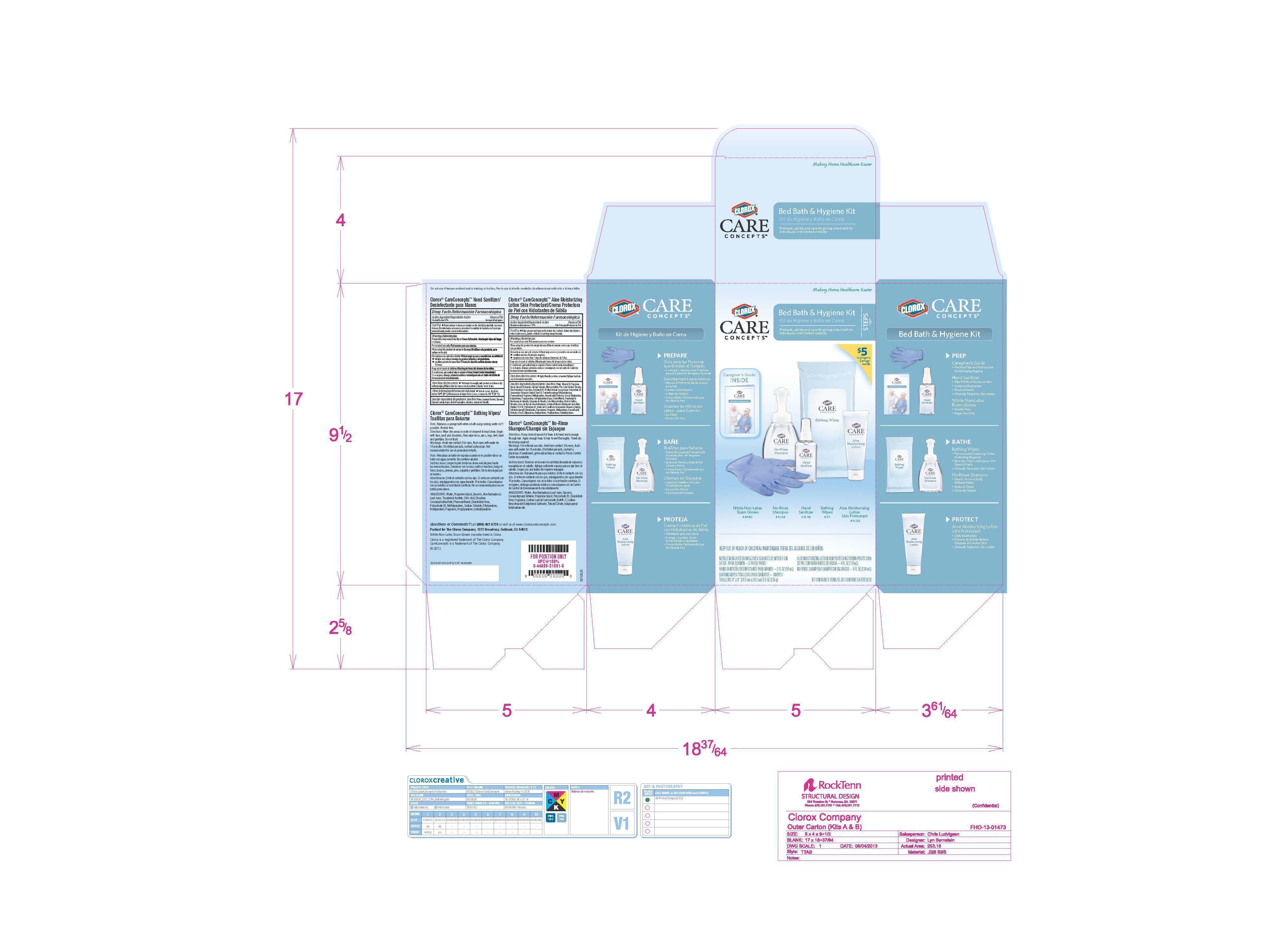 DRUG LABEL: Clorox CareConcepts Bed Bath and Hygiene
NDC: 26509-0007 | Form: KIT | Route: TOPICAL
Manufacturer: The Clorox Company
Category: otc | Type: HUMAN OTC DRUG LABEL
Date: 20140821

ACTIVE INGREDIENTS: DIMETHICONE 1.25 mg/100 mL; ALCOHOL 67 mL/100 mL
INACTIVE INGREDIENTS: water; MINERAL OIL; PROPYLENE GLYCOL; GLYCERYL DISTEARATE; GLYCERYL STEARATE SE; MICROCRYSTALLINE WAX; CETYL ALCOHOL; glycerin; aloe; (C10-C30)ALKYL METHACRYLATE ESTER; POLYSORBATE 20; JOJOBA OIL; EDETOL; PHENOXYETHANOL; METHYLPARABEN; BENZOTRIAZOLYL DODECYL P-CRESOL; ETHYLPARABEN; BUTYLPARABEN; PROPYLPARABEN; ISOBUTYLPARABEN; water; ISOPROPYL ALCOHOL; glycerin; GLYCERYL LAURATE

Bed Bath and Hygiene Kit

Active Ingredient

Dimethicone 1.25 percent

Purpose

Skin Protectant

Use

- Helps prevent and temporarily protect dry, cracked, chafed skin.

Warnings

For external use only

When using this product do not get into eyes

Keep out of reach of children.

If swallowed, get medical help or contact a Poison Control Center immediately.

Directions

- Apply liberally as often as needed.

Inactive Ingredients

Water, Mineral Oil, Propylene Glycol, Glyceryl Distearate, Glyceryl Stearate, Microcrystalline Wax, Cetyl Alcohol, Glycerin, Aloe Barbadensis Leaf Juice, Acrylates/C10-30 Alkyl Acrylate Crosspolymer, Polysorbate 20, Simmondsia Chinensis (Jojoba) Seed Oil, Tetrahydroxypropyl Ethylenediamine, Phenoyethanol, Fragrance, Methylparaben, Benzatriazoyl Dodecyl p-Cresol, Ethylparaben, Butylparaben, Propylparaben, Isobutylparaben

Active ingredient

Alcohol 67 percent

Purpose

Antiseptic

Use

Hand sanitizer to decrease bacteria on the skin that potentially can cause disease

Warnings

Flammable. Keep away from fire or flame.
For external use only.

When using this product, do not use in the eyes.

Discontinue use and ask a doctor if

- irritate and redness develop.
- condition persists for more than 72 hours.

Keep out of reach of children.

If swallowed, get medical help or contact a Poison Control Center immediately.

Directions

Wet hands thoroughly with product and allow to dry without wiping.

Other Information

Store in a cool, dry place below 104 deg F (40 deg C).

Inactive ingredients

Water, Isopropyl Alcohol, Glycerin, Glyceryl Laurate.

PACKAGE LABEL

Clorox Care Concepts
Bed Bath and Hygiene Kit
Nitrile Non-Latex Exam Gloves
No-Rinse Shampoo
Hand Sanitizer
Bathing Wipes
Aloe Moisturizing Lotion Skin Protectant